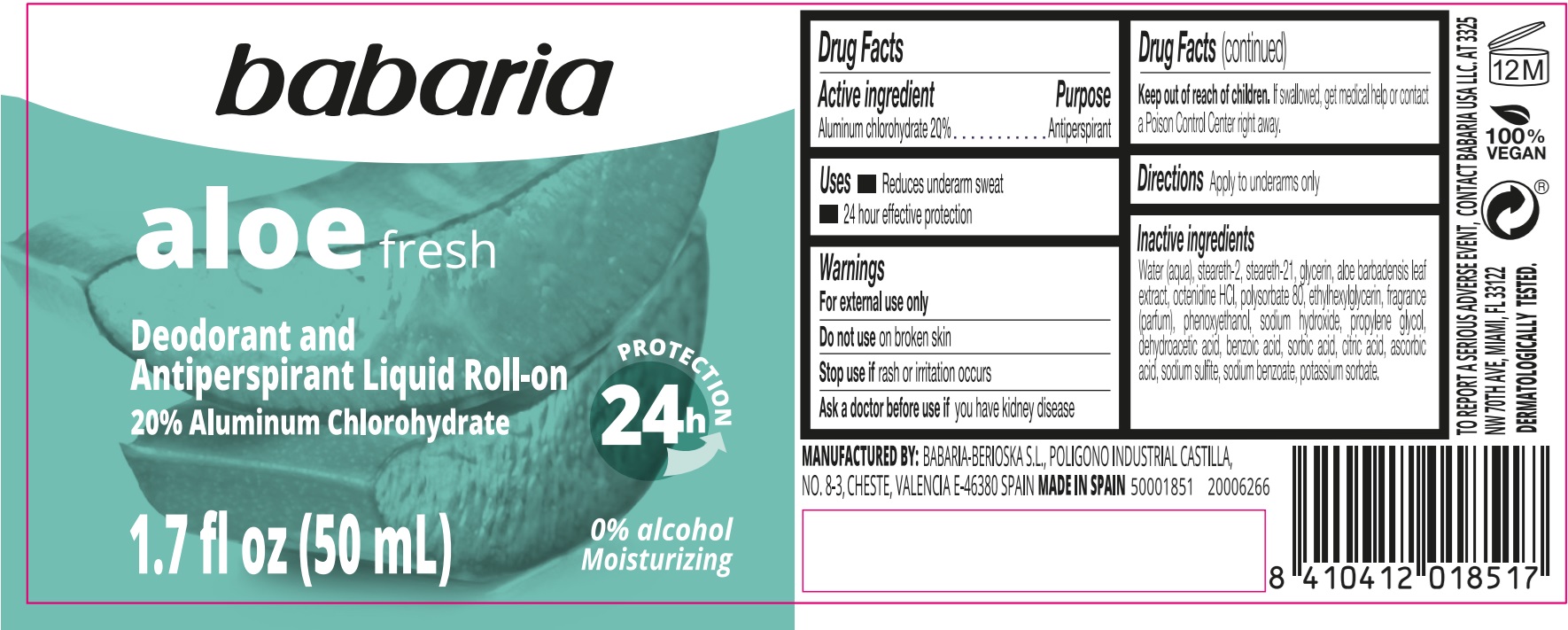 DRUG LABEL: Babaria Aloe Fresh Deodorant and Antiperspirant Liquid Roll-On
NDC: 78283-001 | Form: EMULSION
Manufacturer: BERIOSKA SL
Category: otc | Type: HUMAN OTC DRUG LABEL
Date: 20251216

ACTIVE INGREDIENTS: ALUMINUM CHLOROHYDRATE 200 mg/1 mL
INACTIVE INGREDIENTS: WATER; STEARETH-2; STEARETH-21; GLYCERIN; ALOE VERA LEAF; OCTENIDINE HYDROCHLORIDE; POLYSORBATE 80; ETHYLHEXYLGLYCERIN; PHENOXYETHANOL; SODIUM HYDROXIDE; PROPYLENE GLYCOL; DEHYDROACETIC ACID; BENZOIC ACID; SORBIC ACID; CITRIC ACID MONOHYDRATE; ASCORBIC ACID; SODIUM SULFITE; SODIUM BENZOATE; POTASSIUM SORBATE

Babaria Aloe Fresh Deodorant and Antiperspirant Liquid Roll-On

Active ingredient

Aluminum chlorohydrate 20%

Purpose

Antiperspirant

Uses

- Reduces underarm sweat
- 24 hour effective protection

Warnings

For external use only

Do not use

on broken skin

Stop use if

rash or irritation occurs

Ask a doctor before use if

you have kidney disease

Keep out of reach of children.

If swallowed, get medical help or contact a Poison Control Center right away.

Directions

Apply to underarms only

Inactive ingredients

Water (aqua), steareth-2, steareth-21, glycerin, aloe barbadensis leaf extract, octenidine HCL, polysorbate 80, ethylhexylglycerin, fragrance (parfum), phenoxyethanol, sodium hydroxide, propylene glycol, dehydroacetic acid, benzoic acid, sorbic acid, citric acid, ascorbic acid, sodium sulfite, sodium benzoate, potassium sorbate.